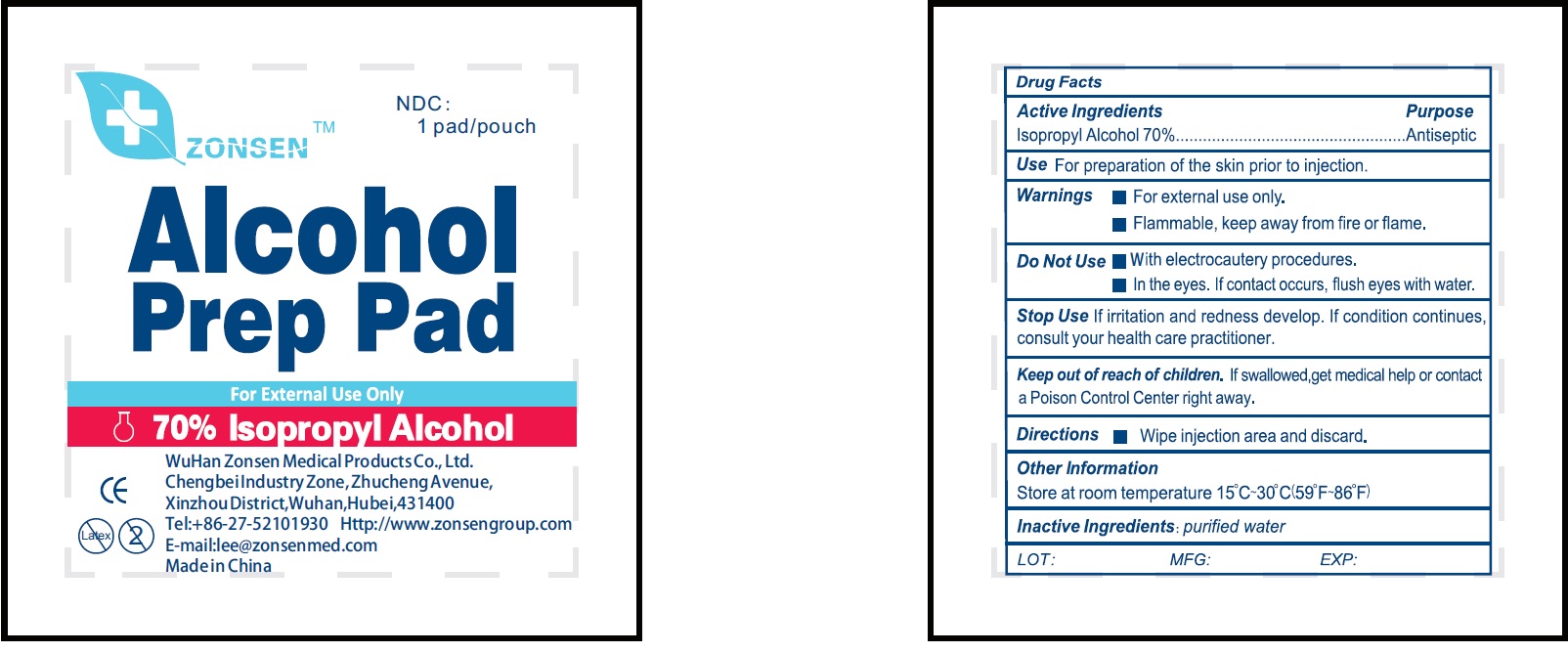 DRUG LABEL: Zonsen Alcohol Prep Pad
NDC: 72932-001 | Form: SWAB
Manufacturer: Wuhan Zonsen Medical Products Co., Ltd.
Category: otc | Type: HUMAN OTC DRUG LABEL
Date: 20190520

ACTIVE INGREDIENTS: ISOPROPYL ALCOHOL 0.7 mL/1 mL
INACTIVE INGREDIENTS: WATER

Zonsen Alcohol Prep Pad

Active Ingredients

Isopropyl Alcohol 70%

Purpose

Antiseptic

Use

For preparation of ths skin prior to injection.

Warnings

- For external use only.
- Flammable, keep away from fire or flame.

Do Not Use

- With electrocautery procedures.
- In the eyes. If contact occurs, flush eyes with water.

Stop Use

If irritation and redness develop. If condition continues, consult your health care practitioner.

Keep out of reach of children.

If swallowed, get medical help or contact a Poison Control Center right away.

Directions

- Wipe injection area and discard.

Other information

Store at room temperature 15°C-30°C(59°F-86°F)

Inactive Ingredients:

purified water